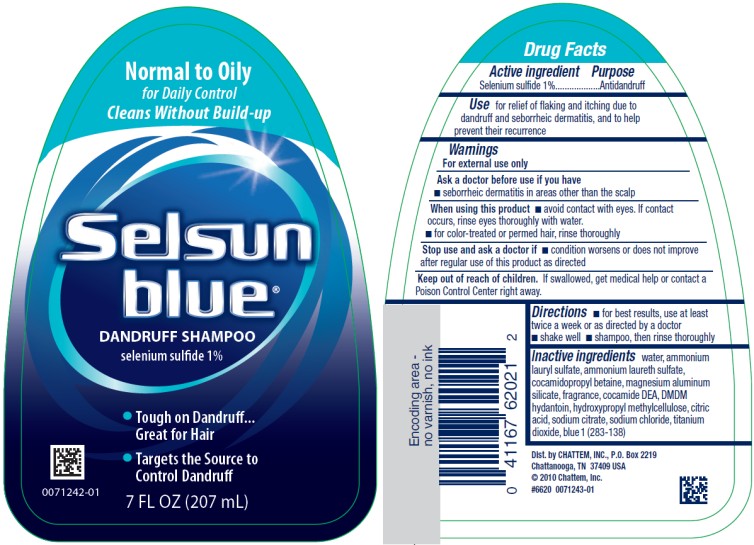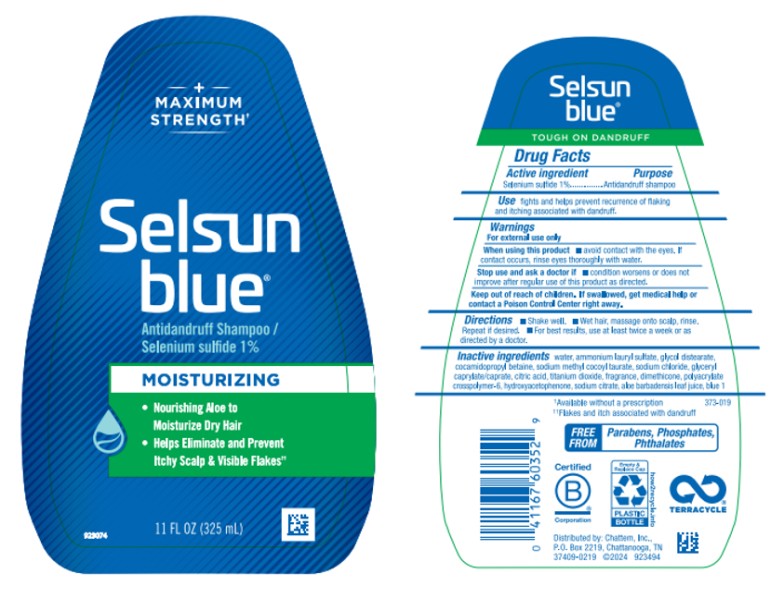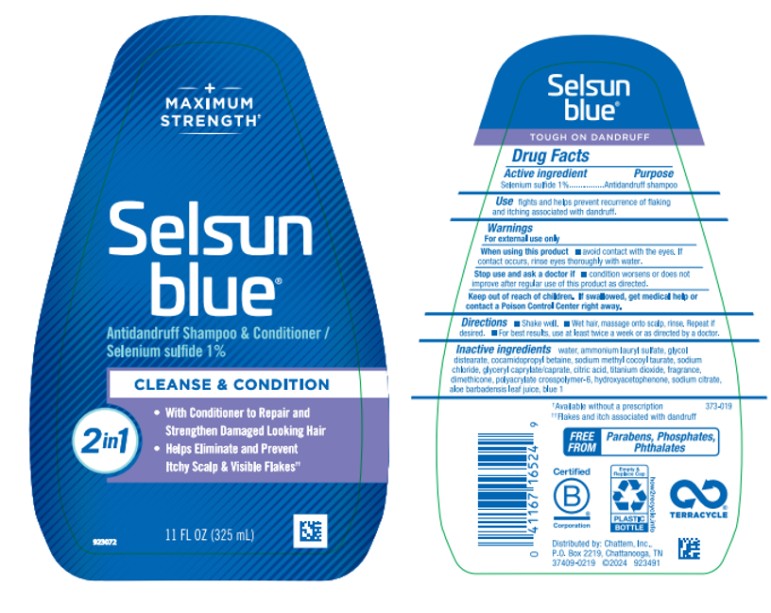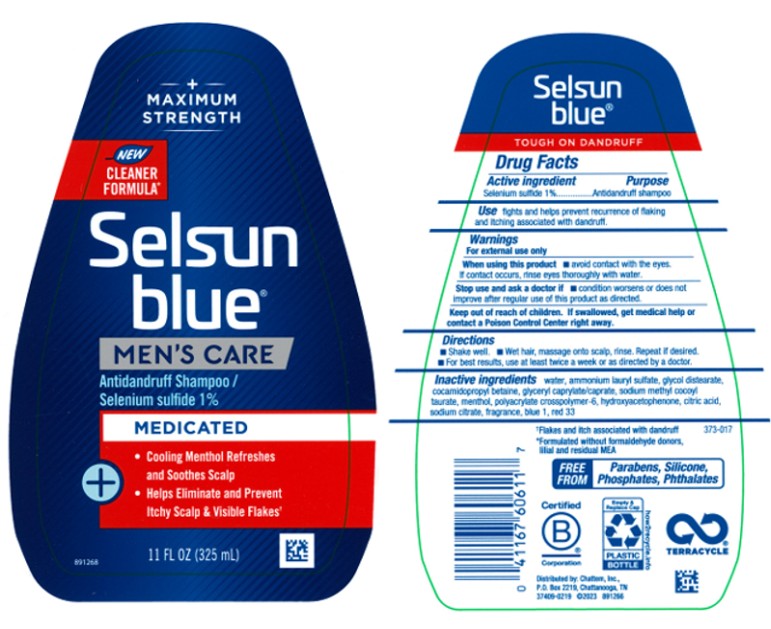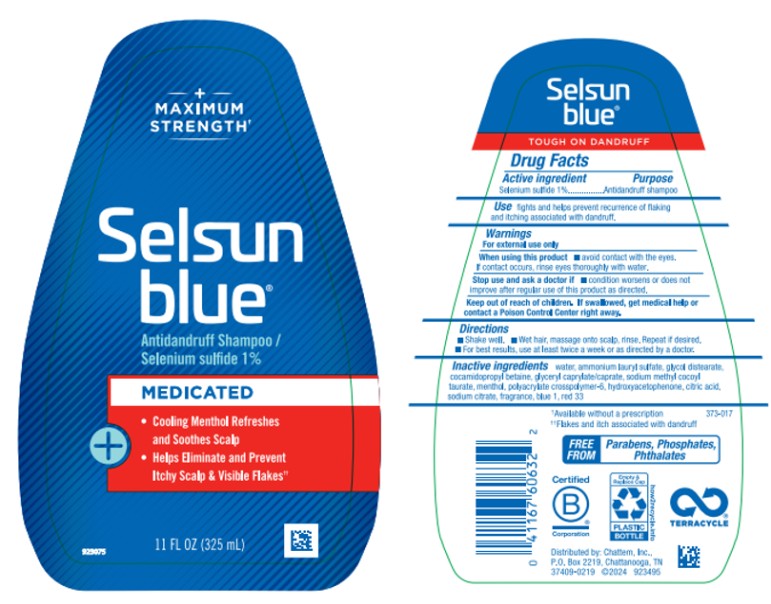 DRUG LABEL: Selsun Blue Normal to Oily
NDC: 41167-6202 | Form: SHAMPOO
Manufacturer: Chattem, Inc.
Category: otc | Type: HUMAN OTC DRUG LABEL
Date: 20260218

ACTIVE INGREDIENTS: SELENIUM SULFIDE 1 g/100 mL
INACTIVE INGREDIENTS: WATER; AMMONIUM LAURYL SULFATE; AMMONIUM LAURETH-3 SULFATE; COCAMIDOPROPYL BETAINE; MAGNESIUM ALUMINUM SILICATE; COCO DIETHANOLAMIDE; DMDM HYDANTOIN; HYPROMELLOSE, UNSPECIFIED; CITRIC ACID MONOHYDRATE; SODIUM CITRATE; SODIUM CHLORIDE; TITANIUM DIOXIDE; FD&C BLUE NO. 1

Selsun Blue

Drug Facts
Selsun Blue Normal to Oily

Active ingredient

Selenium sulfide 1%

Purpose

Antidandruff

Use

Fights and helps prevent recurrence of flaking and itching due to dandruff

Warnings

For external use only

When using this product

- avoid contact with eyes. If contact occurs, rinse eyes thoroughly with water.

Stop use and ask a doctor if

- condition worsens or does not improve after regular use of this product as directed

Keep out of reach of children.

If swallowed, get medical help or contact a Poison Control Center right away.

Directions

- Shake well.
- Wet hair, massage onto scalp, rinse. Repeat if desired.
- For best results, use at least twice a week or as directed by a doctor.

Inactive ingredients

water, ammonium lauryl sulfate, ammonium laureth sulfate, cocamidopropyl betaine, magnesium aluminum silicate, fragrance, cocamide DEA, DMDM hydantoin, hydroxypropyl methylcellulose, citric acid, sodium citrate, sodium chloride, titanium dioxide, blue 1 (283-138)

Drug Facts
Selsun Blue Moisturizing

Active ingredient

Selenium sulfide 1%

Purpose

Antidandruff

Use

Fights and helps prevent recurrence of flaking and itching associated with dandruff

Warnings

For external use only

When using this product

- avoid contact with eyes. If contact occurs, rinse eyes thoroughly with water.

Stop use and ask a doctor if

- condition worsens or does not improve after regular use of this product as directed

Keep out of reach of children.

If swallowed, get medical help or contact a Poison Control Center right away.

Directions

- Shake well.
- Wet hair, massage onto scalp, rinse. Repeat if desired.
- For best results, use at least twice a week or as directed by a doctor.

Inactive ingredients

water, ammonium lauryl sulfate, glycol distearate, cocamidopropyl betaine, sodium methyl cocoyl taurate, sodium chloride, glyceryl caprylate/caprate, citric acid, titanium dioxide, fragrance, dimethicone, polyacrylate crosspolymer-6, hydroxyacetophenone, sodium citrate, aloe barbadensis leaf juice, blue 1

Drug Facts
Selsun Blue 2-in-1

Active ingredient

Selenium sulfide 1%

Purpose

Antidandruff

Use

Fights and helps prevent recurrence of flaking and itching associated with dandruff

Warnings

For external use only

When using this product

- avoid contact with eyes. If contact occurs, rinse eyes thoroughly with water.

Stop use and ask a doctor if

- condition worsens or does not improve after regular use of this product as directed

Keep out of reach of children.

If swallowed, get medical help or contact a Poison Control Center right away.

Directions

- Shake well.
- Wet hair, massage onto scalp, rinse. Repeat if desired.
- For best results, use at least twice a week or as directed by a doctor.

Inactive ingredients

water, ammonium lauryl sulfate, glycol distearate, cocamidopropyl betaine, sodium methyl cocoyl taurate, sodium chloride, glyceryl caprylate/caprate, citric acid, titanium dioxide, fragrance, dimethicone, polyacrylate crosspolymer-6, hydroxyacetophenone, sodium citrate, aloe barbadensis leaf juice, blue 1

Drug Facts
Selsun Blue Medicated

Active ingredient

Selenium sulfide 1%

Purpose

Antidandruff

Use

Fights and helps prevent recurrence of flaking and itching associated with dandruff.

Warnings

For external use only

When using this product

- avoid contact with eyes. If contact occurs, rinse eyes thoroughly with water.

Stop use and ask a doctor if

- condition worsens or does not improve after regular use of this product as directed

Keep out of reach of children.

If swallowed, get medical help or contact a Poison Control Center right away.

Directions

- Shake well.
- Wet hair, massage onto scalp, rinse. Repeat if desired.
- For best results, use at least twice a week or as directed by a doctor.

Inactive ingredients

water, ammonium lauryl sulfate, glycol distearate, cocamidopropyl betaine, glyceryl caprylate/caprate, sodium methyl cocoyl taurate, menthol, polyacrylate crosspolymer-6, hydroxyacetophenone, citric acid, sodium citrate, fragrance, blue 1, red 33

PRINCIPAL DISPLAY PANEL

Normal to Oily
for Daily Control
Cleans Without Build-up
Selsun blue®
DANDRUFF SHAMPOO
selenium sulfide 1%
Tough on Dandruff…Great for Hair
Targets the Source to Control Dandruff
7 FL OZ (207 mL)

PRINCIPAL DISPLAY PANEL

+
MAXIMUM
STRENGTH
Selsun
blue®
Antidandruff Shampoo/
Selenium sulfide 1%
MOISTURIZING
11 FL OZ (325 mL)

PRINCIPAL DISPLAY PANEL

+
MAXIMUM
STRENGTH
Selsun
blue®
Antidandruff Shampoo & Conditioner/
Selenium sulfide 1%
CLEANSE & CONDITION
11 FL OZ (325 mL)

PRINCIPAL DISPLAY PANEL

+
MAXIMUM
STRENGTH
Selsun
blue®
MEN’S CARE
Antidandruff Shampoo/
Selenium sulfide 1%
MEDICATED
11 FL OZ (325 mL)

PRINCIPAL DISPLAY PANEL

+
MAXIMUM
STRENGTH
Selsun
blue®
Antidandruff Shampoo/
Selenium sulfide 1%
MEDICATED
11 FL OZ (325 mL)